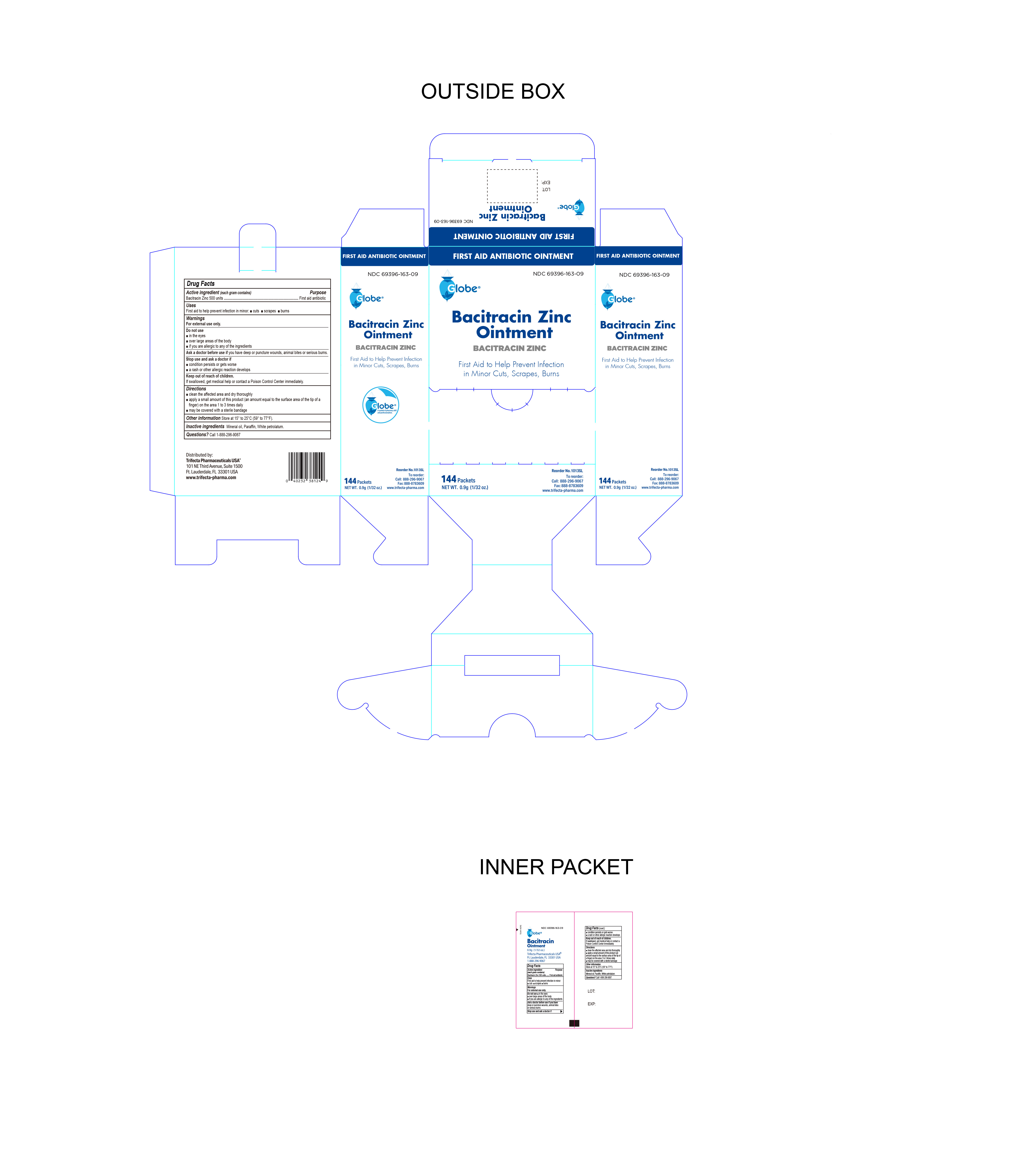 DRUG LABEL: Bacitracin Zinc
NDC: 69396-163 | Form: OINTMENT
Manufacturer: Trifecta Pharmaceuticals USA LLC
Category: otc | Type: HUMAN OTC DRUG LABEL
Date: 20251111

ACTIVE INGREDIENTS: BACITRACIN ZINC 500 [USP'U]/1 g
INACTIVE INGREDIENTS: PARAFFIN; WHITE PETROLATUM; MINERAL OIL

Globe Bacitracin Zinc Ointment

Active Ingredient

Bacitracin Zinc 500 Units

Purpose

First Aid Antibiotic

Uses

First Aid to help prevent infection in

- minor cuts
- scrapes
- burns

Warnings

For External Use Only.

Do Not Use

- in eyes
- over large areas of the body
- if you are allergic to any of the ingredients

Stop Use and Ask Doctor if

- The condition persists or gets worse
- A rash or allergic reaction develops

Directions

- Clean the affected area and dry thoroughly.
- Apply a small amount of the product (an amount equal to the surface area of the tip of a finger) on the area 1 to 3 times daily
- May be covered with a sterile bandage

ASK DOCTOR BEFORE USE IF

you have deep or puncture wounds, aniimal bites or serious burns.

Keep out of reach of children

If swallowed, get medical help or contact a Poison Control Center Immediately.

Inactive Ingredients

Mineral oil, white petrolatum, paraffin

Questions

Call 1-888-296-9067

Fax: 1-888-878-3609

Online: www.trifecta-pharma.com

Reorder No. 1013SL

Storage Information

Store at room temperature 15° to 25°C (59° to 77°F).

Other Information

Distributed By:

Trifecta Pharmaceuticals USA®

Ft. Lauderdale, FL. 33301 USA

www.trifecta-pharma.com